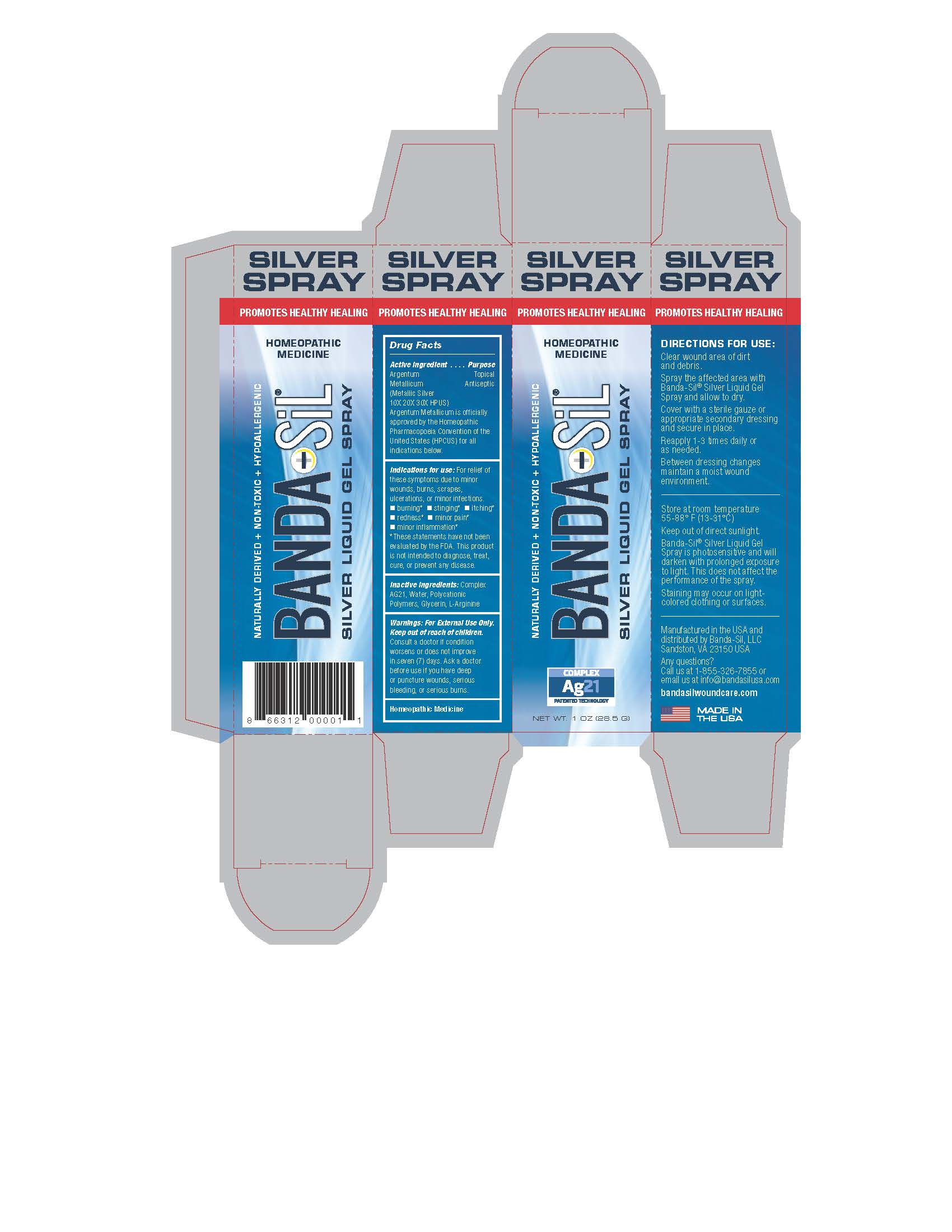 DRUG LABEL: Banda-Sil Liquid Gel
NDC: 72363-005 | Form: GEL
Manufacturer: AG Essence Inc
Category: homeopathic | Type: HUMAN OTC DRUG LABEL
Date: 20240419

ACTIVE INGREDIENTS: SILVER 1 g/28.5 g
INACTIVE INGREDIENTS: WATER 27.13 g/28.5 g; GLYCERIN 0.285 g/28.5 g; ARGININE 0.085 g/28.5 g

DOSAGE AND ADMINISTRATION

Directions For Use:

Clear wound area of dirt and debris.

Spray the affected area with Banda-Sil Silver Liquid Gel Spray and allow to dry.

Cover with a sterile gauze or appropriate secondary dressing and secure in place.

Reapply 1-3 times daily or as needed.

Between dressing changes maintain a moist wound environment.

Warnings:

For External Use Only. Keep out of reach of children.

Consult a doctor if condition worsens or does not improve in seven (7) days. Ask a doctor before use if you have deep or puncture wounds, serious bleeding, or servious burns.

Inactive Ingredients:

Complex AG21, Water, Polycationic Polymers, Glycerin, L-Arginine

Indications for use:

For relief of these symptoms due to minor wounds, burns, scrapes ulcerations,or minor infections, burning, stinging, itching, redness, minor pain, minor inflammation.

Warnings:

For External Use Only. Keep out of reach of children.

PURPOSE

Topical Antiseptic

Active Ingredient

Argentum Metallicum (Metallic Silver 10X 20X 30X HPUS)